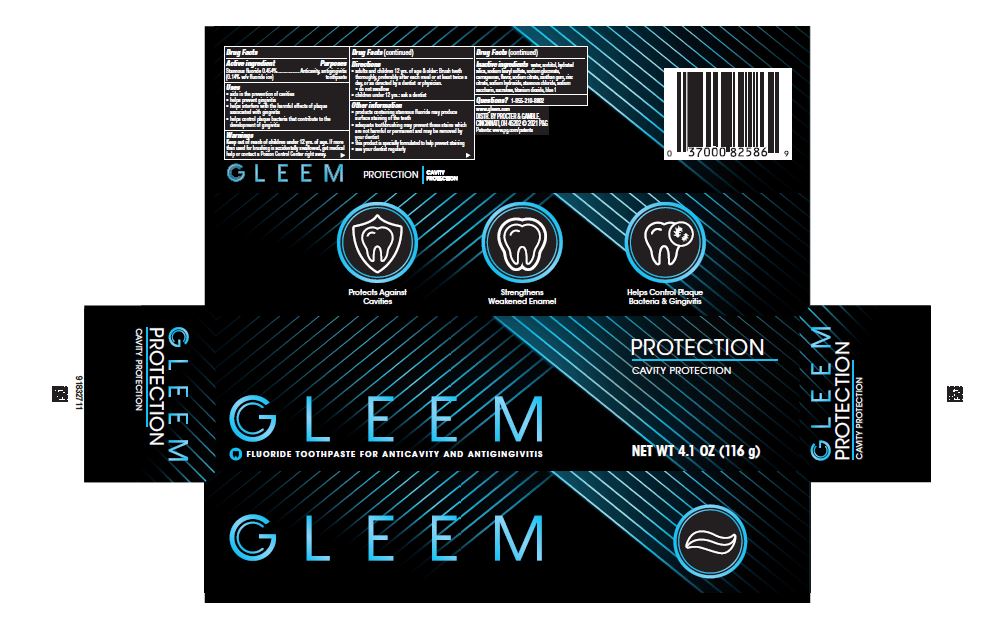 DRUG LABEL: GLEEM
NDC: 69423-908 | Form: PASTE, DENTIFRICE
Manufacturer: The Procter & Gamble Manufacturing Company
Category: otc | Type: HUMAN OTC DRUG LABEL
Date: 20250806

ACTIVE INGREDIENTS: STANNOUS FLUORIDE 1.4 mg/1 g
INACTIVE INGREDIENTS: STANNOUS CHLORIDE; SUCRALOSE; HYDRATED SILICA; SORBITOL; SODIUM CITRATE; ZINC CITRATE; WATER; SODIUM LAURYL SULFATE; SODIUM GLUCONATE; CARRAGEENAN; SACCHARIN SODIUM; XANTHAN GUM; TITANIUM DIOXIDE; SODIUM HYDROXIDE; FD&C BLUE NO. 1

GLEEM Protection

Drug Facts

Active ingredient

Stannous fluoride 0.454% (0.14% w/v fluoride ion)

Purposes

Anticavity, antigingivitis toothpaste

Uses

- aids in the prevention of cavities
- helps prevent gingivitis
- helps interfere with the harmful effects of plaque associated with gingivitis
- helps control plaque bacteria that contribute to the development of gingivitis

Warnings

Keep out of reach of children under 12 yrs. of age. If more than used for brushing is accidentally swallowed, get medical help or contact a Poison Control Center right away.

Directions

- adults and children 12 yrs. of age & older: Brush teeth thoroughly, preferably after each meal or at least twice a day, or as directed by a dentist or physician.
- do not swallow
- children under 12 yrs.: ask a dentist

Other information

- products containing stannous fluoride may produce surface staining of the teeth
- adequate toothbrushing may prevent these stains which are not harmful or permanent and may be removed by your dentist
- this product is specially formulated to help prevent staining
- see your dentist regularly

Inactive ingredients

water, sorbitol, hydrated silica, sodium lauryl sulfate, sodium gluconate, carrageenan, flavor, sodium citrate, xanthan gum, zinc citrate, sodium hydroxide, stannous chloride, sodium saccharin, sucralose, titanium dioxide, blue 1

Questions?

1-855-510-8802

DISTR. BY PROCTER & GAMBLE,
CINCINNATI, OH 45202

PRINCIPAL DISPLAY PANEL - 99 g Tube Carton

GLEEM

FLUORIDE TOOTHPASTE FOR ANTICAVITY AND ANTIGINGIVITIS

PROTECTION

CAVITY PROTECTION

NET WT 4.1 OZ (116 g)